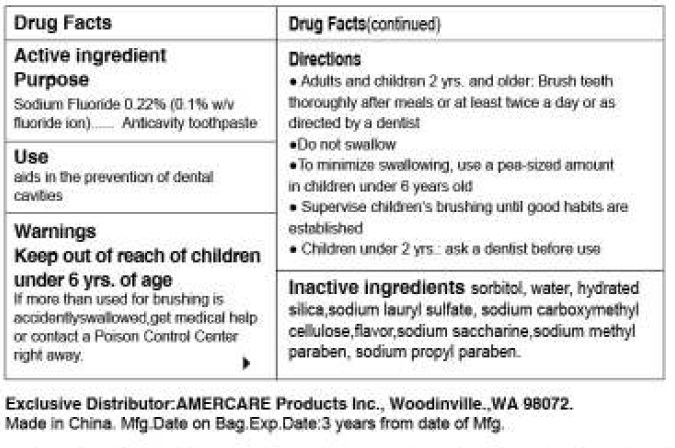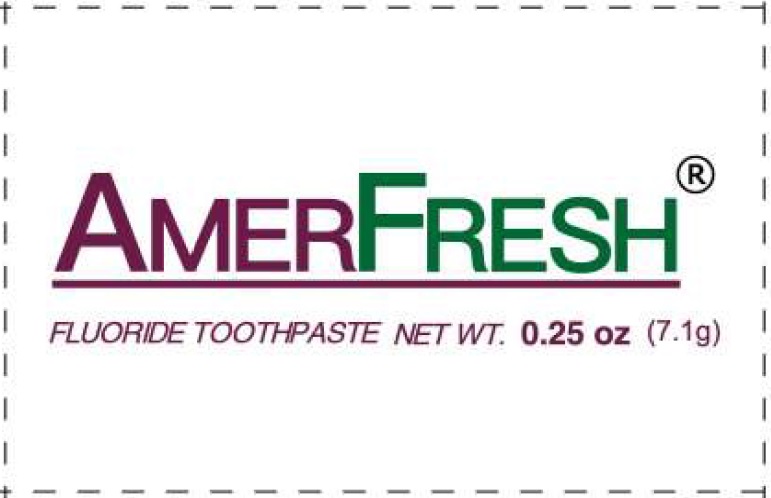 DRUG LABEL: Amerfresh Fluoride
NDC: 51460-3030 | Form: PASTE
Manufacturer: Amercare Products, Inc.
Category: otc | Type: HUMAN OTC DRUG LABEL
Date: 20161018

ACTIVE INGREDIENTS: SODIUM FLUORIDE 2.2 mg/1 g
INACTIVE INGREDIENTS: SORBITOL; WATER; HYDRATED SILICA; SODIUM LAURYL SULFATE; CARBOXYMETHYLCELLULOSE SODIUM, UNSPECIFIED FORM; SACCHARIN SODIUM; METHYLPARABEN SODIUM; PROPYLPARABEN SODIUM

Amerfresh Fluoride

Active Ingredient

Sodium Fluoride 0.22% (0.1% w/v fluoride ion)

Purpose

Anticavity toothpaste

Use

aids prevention of dental cavities

Warnings

Keep out of reach of children under 6 yrs. of age

If more than used for brushing is accidentally swallowed, get medical help or contact a Poison Control Center right away.

Directions

- Adults and children 2 yrs. and older: Brush teeth thoroughly after meals or at least twice a day or as directed by a dentist.
- Do not swallow
- To minimize swallowing, use a pea-sized amount in children under 6 years old
- Supervise children's brushing until good habits are established
- Children under 2 yrs: ask a dentist before use

Inactive Ingredients

sorbitol, water, hydrated silica, sodium lauryl sulfate, sodium carboxymethyl cellulose, flavor, sodium saccharine, sodium methyl paraben, sodium propyl paraben.